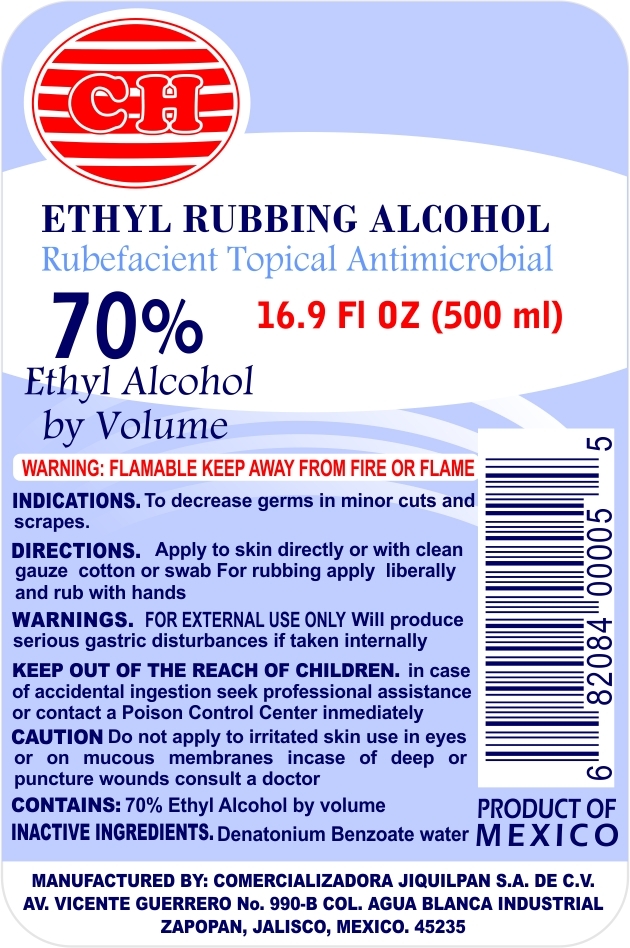 DRUG LABEL: ETHYL RUBBING ALCOHOL
NDC: 15231-100 | Form: LIQUID
Manufacturer: COMERCIALIZADORA JIQUILPAN S.A. DE C.V.
Category: otc | Type: HUMAN OTC DRUG LABEL
Date: 20110605

ACTIVE INGREDIENTS: ALCOHOL 70 mL/100 mL
INACTIVE INGREDIENTS: WATER 29.65 mL/100 mL; DENATONIUM BENZOATE ANHYDROUS .35 mg/100 mL

MAIN LABEL

ACTIVE INGREDIENT

CONTAINS:70% Ethyl Alcohol by volume

as per label.jpg

PURPOSE

INDICATIONS. To decrease germs in minor cuts and scrapes

as per label.jpg

DOSAGE AND ADMINISTRATION

DIRECTIONS. Apply to skin directly or with clean gauze cotton or swab For rubbing apply liberally and rub with hands.

as per label.jpg

WARNINGS

WARNINGS.FOR EXTERNAL USE ONLY Will produce serious gastric disturbances if taken internally

as per label.jpg

KEEP OUT OF REACH OF CHILDREN

KEEP OUT OF THE REACH OF CHILDREN. In case of accidental ingestion seek professional assistance or contact a Poison Control Center inmediately

as per label.jpg

INDICATIONS AND USAGE

CAUTION Do not apply to irritated skin use in eyes or on mucous membranes incase of deep or puncture wounds consult a doctor

as per label.jpg

INACTIVE INGREDIENTS .Denatonium Benzoate water

as per label.jpg

label. jpg